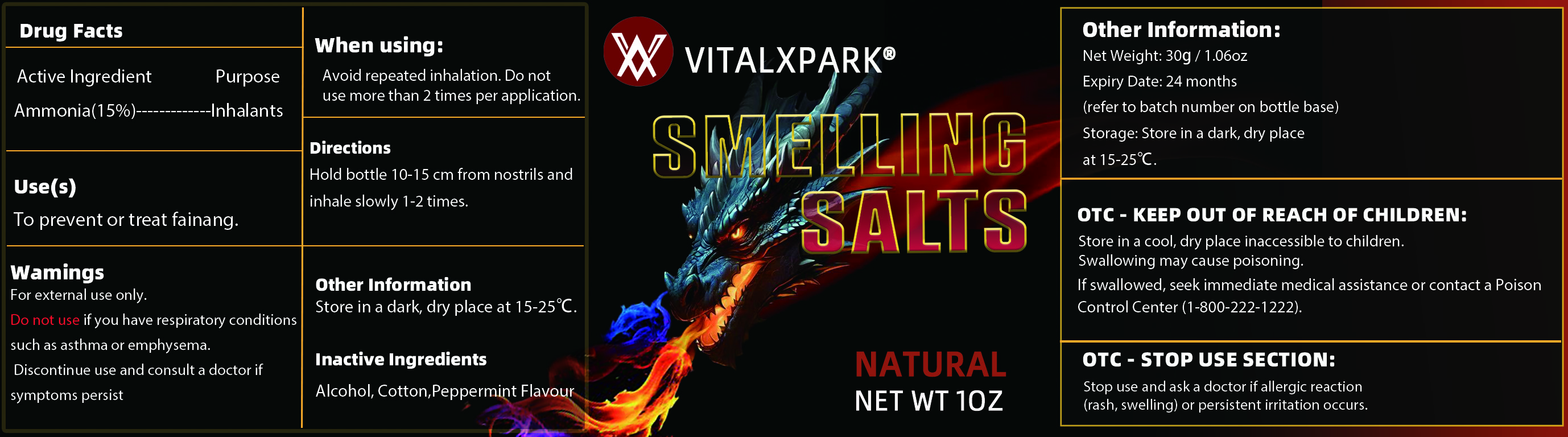 DRUG LABEL: Smelling Salts
NDC: 85821-001 | Form: INHALANT
Manufacturer: Shenzhen Weikeduo E-commerce Co., Ltd.
Category: otc | Type: HUMAN OTC DRUG LABEL
Date: 20250718

ACTIVE INGREDIENTS: AMMONIA 15 g/100 g
INACTIVE INGREDIENTS: PEPPERMINT; ALCOHOL; COTTON

ACTIVE INGREDIENT

Ammonia 15%

PURPOSE

Inhalants

INDICATIONS AND USAGE

To prevent or treat fainang.

WARNINGS

For external use only.

Do not use if you have respiratory conditions such as asthma or emphysema. Discontinue use and consult a doctor if symptoms persist

WHEN USING

Avoid repeated inhalation. Do not use more than 2 times per application.

Stop use and ask a doctor if allergic reaction (rash, swelling) or persistent irritation occurs.

KEEP OUT OF REACH OF CHILDREN: Store in a cool, dry place inaccessible to children. Swallowing may cause poisoning. If swallowed, seek immediate medical assistance or contact a Poison Control Center (1-800-222-1222).

DOSAGE AND ADMINISTRATION

Hold bottle 10-15 cm from nostrils and inhale slowly 1-2 times.

STORAGE AND HANDLING

Store in a cool, dry place inaccessible to children.

INACTIVE INGREDIENT

Alcohol, Cotton, Peppermint Flavour